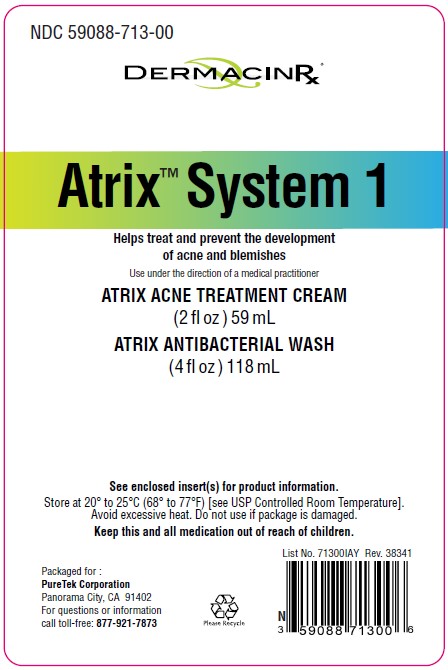 DRUG LABEL: Atrix System 1
NDC: 59088-713 | Form: KIT | Route: TOPICAL
Manufacturer: PureTek Corporation
Category: otc | Type: HUMAN OTC DRUG LABEL
Date: 20241213

ACTIVE INGREDIENTS: SALICYLIC ACID 20 mg/1 mL; SALICYLIC ACID 20 mg/1 mL
INACTIVE INGREDIENTS: CARBOMER HOMOPOLYMER, UNSPECIFIED TYPE; WATER; GLUCOSAMINE HYDROCHLORIDE; CYCLOMETHICONE 5; CAPRYLYL GLYCOL; STEARIC ACID; .ALPHA.-TOCOPHEROL ACETATE, DL-; BUTYLENE GLYCOL; DIMETHICONE; CETEARYL OLIVATE; OLIGOPEPTIDE-10; PHENOXYETHANOL; DECYL GLUCOSIDE; SACCHAROMYCES CEREVISIAE; SODIUM ASCORBYL PHOSPHATE; UREA; .ALPHA.-GLUCAN OLIGOSACCHARIDE; GLYCYRRHIZINATE DIPOTASSIUM; EDETATE DISODIUM; ETHYLHEXYLGLYCERIN; HEXYLENE GLYCOL; SODIUM HYDROXIDE; GLYCERIN; GLYCERYL STEARATE SE; DIMETHICONE/VINYL DIMETHICONE CROSSPOLYMER (SOFT PARTICLE); SORBITAN OLIVATE; PALMITIC ACID; LAMINARIA DIGITATA; ALLYL METHACRYLATE/GLYCOL DIMETHACRYLATE CROSSPOLYMER; GRAPEFRUIT OIL; EDETATE DISODIUM; GLYCERIN; MENTHYL LACTATE, (-)-; APPLE; ROSEMARY; .ALPHA.-IONENE; COCAMIDOPROPYL BETAINE; EUROPEAN ELDERBERRY; WATER; CETYL HYDROXYETHYLCELLULOSE (350000 MW); LAURYL GLUCOSIDE; MENTHOL, UNSPECIFIED FORM; SODIUM LAURYL GLYCOL CARBOXYLATE

AtrixSystem 1
ATRIX ACNE TREATMENT CREAM (2 fl oz) 59 mL
ATRIX ANTIBACTERIAL WASH (4 fl oz) 118 mL
10/19- update marketing date

Active ingredient

Salicylic Acid 2%

Purpose

Acne Treatment

Uses:

■ for the treatment of acne
■ dries and clears acne pimples, acne blemishes, whiteheads and blackheads
■ helps prevent the development of new acne pimples, acne blemishes, whiteheads and blackheads

Warnings

For external use only

When using this product

■ skin irritation and dryness is more likely to occur if you use another topical acne medication at the same time. If irritation occurs, only use one topical acne medication at a time.

■ rinse right away with water if it gets in eyes.

Stop use and ask a doctor

■ if skin irritation occurs or gets worse

Keep out of reach of children.

If swallowed, get medical help or contact a Poison Control Center right away.

Directions

■ Clean the skin thoroughly before applying this product

■ cover the entire affected area with a thin layer one to three times daily

■ because excessive drying of the skin may occur, start with one application daily, then gradually increase to two or three times daily if needed or as directed by a doctor

■ if bothersome dryness or peeling occurs, reduce application to once a day or every other day.

Use under the direction of a medical practitioner.

Other information

■ protect from freezing

■ avoid excessive heat

Store at 15° to 30°C (59° to 86°F) [see USP Controlled Room Temperature].
Avoid excessive heat. Do not use if package is damaged.
Keep this and all medication out of reach of children.

Inactive ingredients

Allyl Methacrylates Crosspolymer, Aqua (Purified Water), Butylene Glycol, Caprylyl Glycol, Carbomer, Cetearyl Olivate, Cyclopentasiloxane, Decyl Glucoside, Dimethicone, Dipotassium Glycyrrhizinate, Disodium EDTA, Ethylhexylglycerin, Alpha-Glucan Oligosaccharide, Glucosamine HCl, Glycerin, Glyceryl Stearate SE, Hexylene Glycol, Laminaria Digitata (Algae) Extract, Oligopeptide- 10, Palmitic Acid, Phenoxyethanol, Polysilicone-11, Saccharomyces Cerevisiae Extract, Sodium Ascorbyl Phosphate, Sodium Hydroxide, Sorbitan Olivate, Stearic Acid, DL- alpha- Tocopheryl Acetate, Urea

QUESTIONS

Call toll-free:

1-877-921-7873

Active ingredient

Salicylic Acid 2%

Purpose

Acne treatment

Use

■ for the treatment of acne

■ dries and clears acne pimples, acne blemishes, whiteheads, and blackheads

■ helps prevent the development of new acne pimples, acne blemishes, whiteheads, and blackheads

Warnings

For external use only.

When using this product

■ skin irritation and dryness is more likely to occur if you use another topical acne medication at the same time. If irritation occurs, only use one topical acne medication at a time.

■ rinse right away with water if it gets in eyes.

Stop use and ask a doctor

■ if skin irritation occurs or gets worse

Keep out of reach of children.

If swallowed, get medical help or contact a Poison Control Center right away.

Directions

■ Cleanse twice a day.

■ Wet face. Apply to hands, add water and work into a lather.

■ Massage face gently.
■ Rinse thoroughly and pat dry if bothersome dryness or peeling occurs, reduce application to once a day or every other day.

Use under the direction of a medical practitioner.

Other information

■ protect from freezing

■ avoid excessive heat

Store at 20° to 25°C (68° to 77°F)
[see USP Controlled Room Temperature].

Inactive ingredients

Aqua (Purified Water), Cetyl Hydroxyethylcellulose, Citrus Paradisi (Grapefruit) Peel Oil, Cocamidopropyl Betaine, Disodium EDTA, Ethoxydiglycol, Glycerin, Lauryl Glucoside, Menthol, Menthyl Lactate, Pyrus Malus (Apple) Fruit Extract, Rosmarinus Officinalis (Rosemary) Leaf Extract, Sambucus Nigra (Elderberry) Fruit Extract, Sodium Lauryl Glucose Carboxylate.

Questions?

Call toll-free:

1-877-921-7873